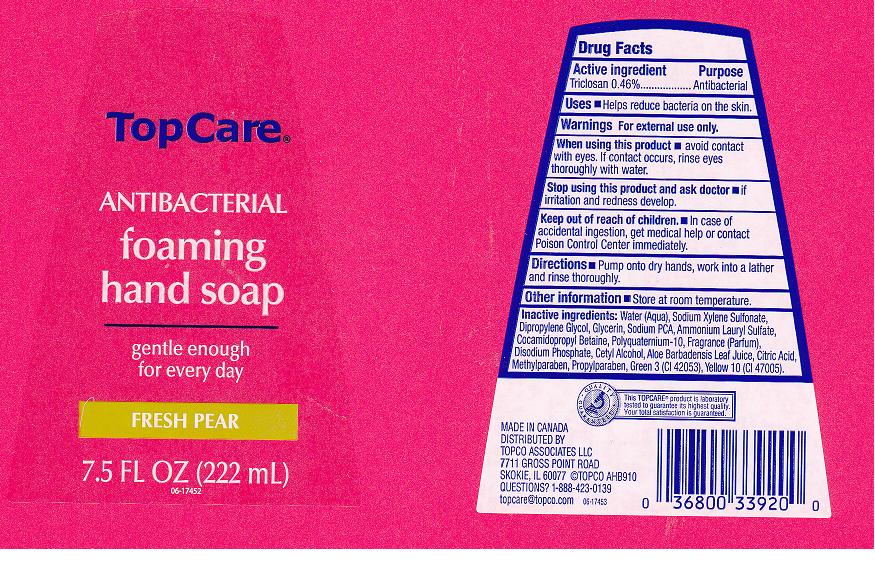 DRUG LABEL: ANTIBACTERIAL
NDC: 36800-184 | Form: SOLUTION
Manufacturer: TOPCO ASSOCIATES LLC
Category: otc | Type: HUMAN OTC DRUG LABEL
Date: 20110802

ACTIVE INGREDIENTS: TRICLOSAN 0.46 mL/100 mL
INACTIVE INGREDIENTS: WATER; SODIUM XYLENESULFONATE; DIPROPYLENE GLYCOL; GLYCERIN; SODIUM PYRROLIDONE CARBOXYLATE; AMMONIUM LAURYL SULFATE; COCAMIDOPROPYL BETAINE; POLYQUATERNIUM-10 (400 CPS AT 2%); SODIUM PHOSPHATE, DIBASIC ANHYDROUS; CETYL ALCOHOL; ALOE VERA LEAF; ANHYDROUS CITRIC ACID; METHYLPARABEN; PROPYLPARABEN; FD&C GREEN NO. 3; D&C YELLOW NO. 10

DRUG FACTS

ACTIVE INGREDIENT

TRICLOSAN 0.46%

PURPOSE

ANTIBACTERIAL

USES

HELPS REDUCE BACTERIA ON THE SKIN

WARNINGS

FOR EXTERNAL USE ONLY

WHEN USING THIS PRODUCT

AVOID CONTACT WITH EYES. IF CONTACT OCCURS, RINSE EYES THOROUGHLY WITH WATER.

STOP USING THIS PRODUCT AND ASK DOCTOR

IF IRRITATION AND REDNESS DEVELOP

KEEP OUT OF REACH OF CHILDREN

IN CASE OF ACCIDENTAL INGESTION, GET MEDICAL HELP OR CONTACT POISON CONTROL CENTER IMMEDIATELY

DIRECTIONS

PUMP ONTO DRY HANDS, WORK INTO LATHER AND RINSE THOROUGHLY.

OTHER INFORMATION

STORE AT ROOM TEMPERATURE

INACTIVE INGREDIENTS

WATER (AQUA), SODIUM XYLENE SULFONATE, DIPROPYLENE GLYCOL, GLYCERIN, SODIUM PCA, AMMONIUM LAURYL SULFATE, COCAMIDOPROPYL BETAINE, POLYQUATERNIUM-10, FRAGRANCE (PARFUM), DISODIUM PHOSPHATE, CETYL ALCOHOL, ALOE BARBADENSIS LEAF JUICE, CITRIC ACID, METHYLPARABEN, PROPYLPARABEN, GREEN 3 (CI 42053), YELLOW 10 (CI47005)